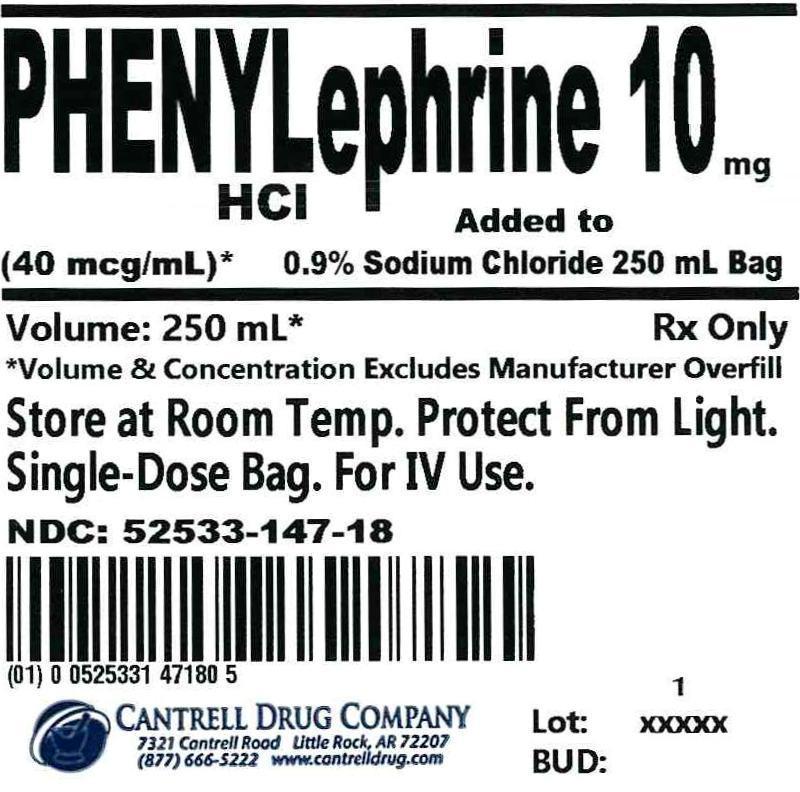 DRUG LABEL: Phenylephrine HCl
NDC: 52533-147 | Form: INJECTION, SOLUTION
Manufacturer: Cantrell Drug Company
Category: prescription | Type: HUMAN PRESCRIPTION DRUG LABEL
Date: 20130430

ACTIVE INGREDIENTS: Phenylephrine Hydrochloride 40 ug/1 mL
INACTIVE INGREDIENTS: Sodium Chloride 9 mg/1 mL; Water

Phenylephrine HCl 10 mg Added to 0.9% Sodium Chloride 250 mL Bag